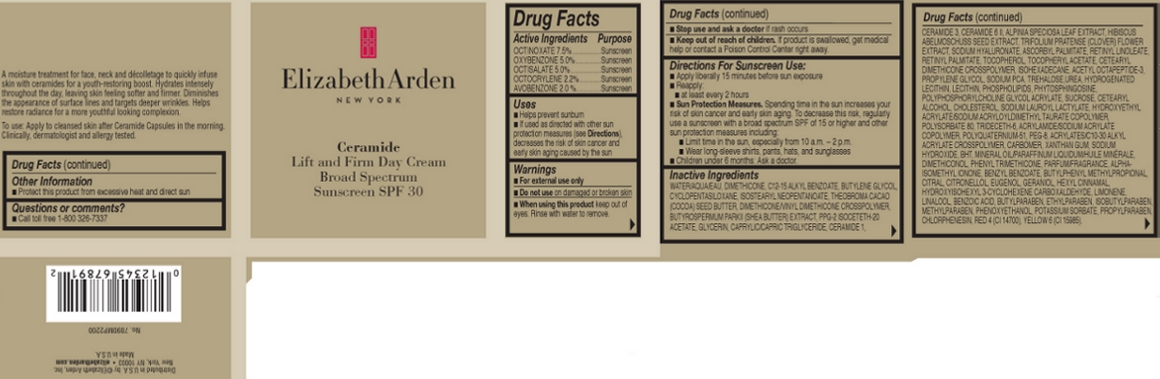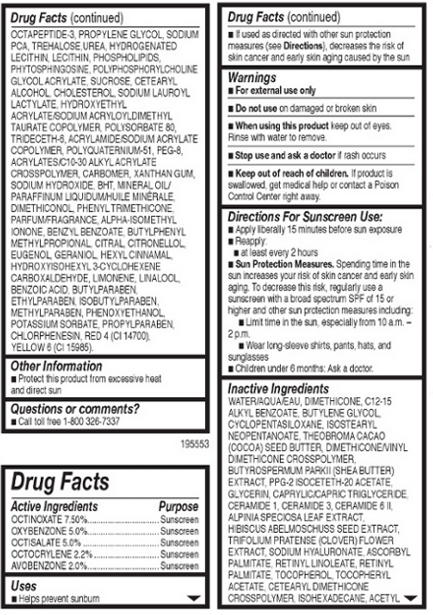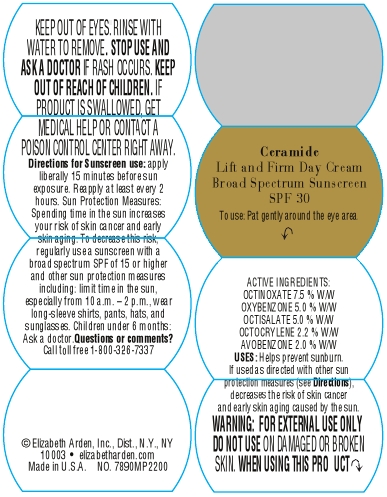 DRUG LABEL: Ceramide Lift And Firm Day Broad Spectrum Sunscreen SPF 30
NDC: 67938-0964 | Form: CREAM
Manufacturer: Elizabeth Arden, Inc
Category: otc | Type: HUMAN OTC DRUG LABEL
Date: 20130418

ACTIVE INGREDIENTS: OCTINOXATE 3.675 g/49 g; OXYBENZONE 2.45 g/49 g; OCTISALATE 2.45 g/49 g; OCTOCRYLENE 1.078 g/49 g; AVOBENZONE 0.98 g/49 g
INACTIVE INGREDIENTS: WATER; DIMETHICONE; ALKYL (C12-15) BENZOATE; BUTYLENE GLYCOL; CYCLOMETHICONE 5; ISOSTEARYL NEOPENTANOATE; COCOA BUTTER; SHEANUT OIL; PPG-2 ISOCETETH-20 ACETATE; GLYCERIN; MEDIUM-CHAIN TRIGLYCERIDES; CERAMIDE 1; CERAMIDE 3; CERAMIDE 6 II; ALPINIA ZERUMBET LEAF; ABELMOSCHUS MOSCHATUS SEED; TRIFOLIUM PRATENSE FLOWER; HYALURONATE SODIUM; ASCORBYL PALMITATE; RETINYL LINOLEATE; VITAMIN A PALMITATE; TOCOPHEROL; .ALPHA.-TOCOPHEROL ACETATE; ISOHEXADECANE; PROPYLENE GLYCOL; SODIUM PYRROLIDONE CARBOXYLATE; TREHALOSE; UREA; HYDROGENATED SOYBEAN LECITHIN; LECITHIN, SOYBEAN; OMEGA-3 FATTY ACIDS; PHYTOSPHINGOSINE; SUCROSE; CETOSTEARYL ALCOHOL; CHOLESTEROL; SODIUM LAUROYL LACTYLATE; HYDROXYETHYL ACRYLATE/SODIUM ACRYLOYLDIMETHYL TAURATE COPOLYMER (45000 MPA.S AT 1%); POLYSORBATE 80; TRIDECETH-6; POLYETHYLENE GLYCOL 400; XANTHAN GUM; SODIUM HYDROXIDE; BUTYLATED HYDROXYTOLUENE; MINERAL OIL; PHENYL TRIMETHICONE; ISOMETHYL-.ALPHA.-IONONE; BENZYL BENZOATE; BUTYLPHENYL METHYLPROPIONAL; CITRAL; .BETA.-CITRONELLOL, (R)-; EUGENOL; GERANIOL; .ALPHA.-HEXYLCINNAMALDEHYDE; HYDROXYISOHEXYL 3-CYCLOHEXENE CARBOXALDEHYDE; BENZOIC ACID; BUTYLPARABEN; ETHYLPARABEN; ISOBUTYLPARABEN; METHYLPARABEN; PHENOXYETHANOL; POTASSIUM SORBATE; PROPYLPARABEN; CHLORPHENESIN; FD&C RED NO. 4; FD&C YELLOW NO. 6

BC0964

DESCRIPTION

A moisture treatment for face, neck, and decolletage to quickly infuse skin with ceramides for a youth-restoring boost. Hydrates intensely throughout the day, leaving skin feeling softer and firmer. Diminishes the appearance of surface lines and targets deeper wrinkles. Helps restore radiance for a more youthful looking complexion.

INDICATIONS AND USAGE

To Use: Apply to cleansed skin after Ceramide Capsules in the morning.

Directions for Sunscreen Use: Apply liberally 15 minutes before sun exposure. Reapply at least ever 2 hours.

Sun Protection Measures: Spending time in the sun increases your risk of skin cancer and early skin aging. To decrease this risk. regularly use a sunscreen with a broad spectrum SPF of 15 or higher and other sun protection measures including: Limit time in the sun, especially from 10 a.m. - 2 p.m.. Wear long-sleeve shirts, pants, hats, and sunglasses.

WARNINGS

For external use only.

Do not use on damaged or broken skin.

When using this product, keep out of eyes. Rinse with water to remove.

Stop use and ask a doctor if rash occurs.

OTC - ACTIVE INGREDIENT

Active Ingredients: Octinoxate 7.5 %, Oxybenzone 5.0%, Octisalate 5.0%, Octocrylene 2.2%, Avobenzone 2.0%.

INACTIVE INGREDIENT

Other Ingredients: Water/Aqua/Eau, Dimethicone, C12-15 Alkyl Benzoate, Butylene Glycol, Cyclopentasiloxane, Isostearyl Neopentanoate, Theobroma Cacao (Cocoa) Seed Butter, Dimethicone/Vinyl Cimethicon Crosspolymer, Butyrospermum Parkii (Shea Butter) Extract, PPG-2 Isoceteth-20 Acetate, Glycerin Caprylic/Capric Triglyceride, Ceramide 1, Ceramide 3, Ceramide 6 II, Apinia Speciosa Leaf Extract, Hibiscus Abelmoschuss Seed Extract, Trifolium Pratense (Clover) Flower Extract, Sodium Hyaluronate, Ascorbyl Palmitate, Retinyl Linoleate Retinyl Plamitate, Tocopherol, Tocopheryl Acetate, Cetearyl Dimethicon Crosspolymer, Isohexadecane, Acetyo Octapeptide-3, Propylene Glycol, Sodium PCA, Trehalose Urea, Hydrogenated Lecithin, Lecithin Phopholipids, Phytosphingosing, Polyphosphorylcholine Glycol Acrylate, Sucrose, Cetearly Alcohol, Cholesterorl, Sodium lauroyl Lactylate, Hydroxyethyl Acrylate/Sodium Acryloyldimethyl Taurate Copolymer, Polysorbate 80, Trideceth-6, Acrylamide/Sodium Acrylate Copolymer, Polyquaternium-51, PEG-8, Acrylates/C10-30 Alkyl Acrylate Crosspolymer, Carbomer, Xanthan Gum, Sodium Hydroxide, BHT, Mineral Oil/Paraddinum Liquid/Huile Minerale, Dimethiconol. Phenyl Trimethicone, Parfum/Fragrance, Alpha-Isomethyl Ionone, Benzyl Benzoate, Butylphenyl Metyhlpropional, Citral, Citronellol, Eugenol, Geraniol, Hexyl Cinnamal Hydroxyisohexyl 3-Cyclohexene Carboxaldehyde, Limonene, Linalool, Benzoic Acid, Butylparaben, Ethylparaben, Isobutylparaben, Methylparaben, Phenoxyethanol, Potassium Sorbate, Propylparaben, Chlorphenesin, Red 4 (CI 14700), Yellow 6 (CI15985).

DOSAGE & ADMINISTRATION

Apply to skin.

OTC - KEEP OUT OF REACH OF CHILDREN

Keep out of reach of children. If product is swallowed, get medical help or contact a Poison Control center immediately.

OTC - PURPOSE

Provides SPF 30 sun protection.

OTC - WHEN USING

Keep out of eyes.